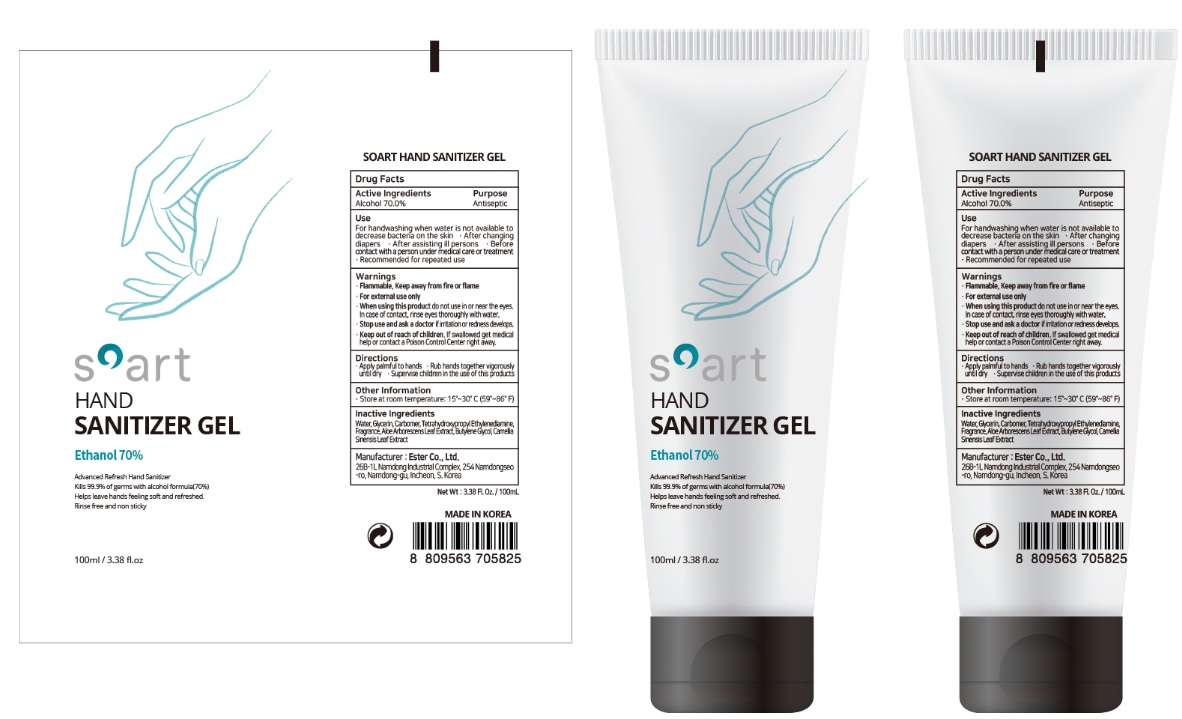 DRUG LABEL: SOART HAND SANITIZER Gel
NDC: 74004-704 | Form: GEL
Manufacturer: Ester Co., Ltd.
Category: otc | Type: HUMAN OTC DRUG LABEL
Date: 20200521

ACTIVE INGREDIENTS: ALCOHOL 70 mL/100 mL
INACTIVE INGREDIENTS: GREEN TEA LEAF; BUTYLENE GLYCOL; EDETOL; CARBOMER HOMOPOLYMER, UNSPECIFIED TYPE; WATER; ALOE ARBORESCENS LEAF; GLYCERIN

[Ester Co., Ltd.-SOART HAND SANITIZER GEL] 100 ml : TUBE : 74004-704-01